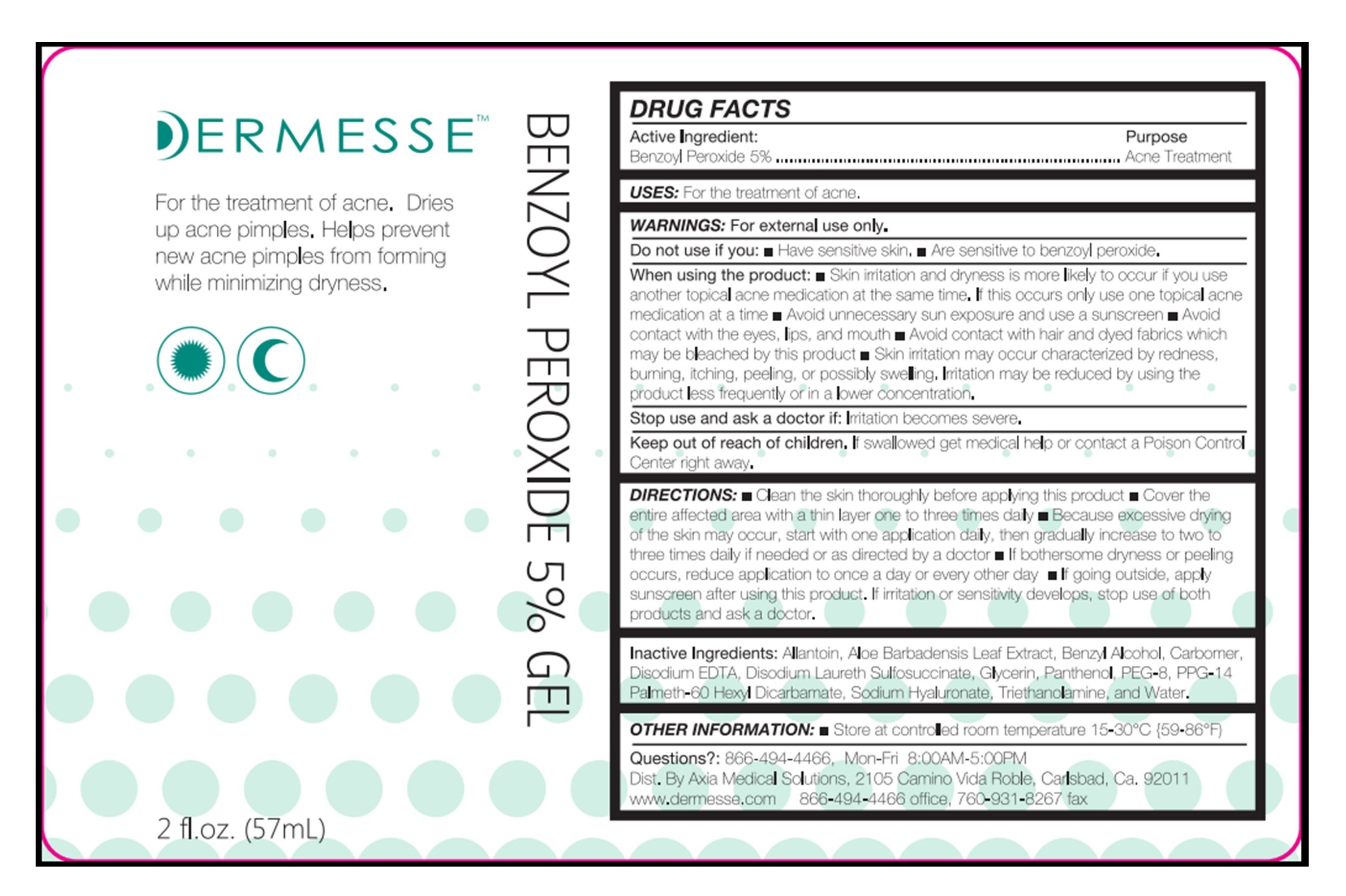 DRUG LABEL: Benzoyl Peroxide 5% Gel
NDC: 68723-305 | Form: GEL
Manufacturer: Axia Medical Solutions, LLC
Category: otc | Type: HUMAN OTC DRUG LABEL
Date: 20210712

ACTIVE INGREDIENTS: BENZOYL PEROXIDE 50 mg/1000 mg
INACTIVE INGREDIENTS: ALLANTOIN; ALOE VERA LEAF; BENZYL ALCOHOL; CARBOMER INTERPOLYMER TYPE A (55000 CPS); EDETATE DISODIUM; DISODIUM LAURETH SULFOSUCCINATE; GLYCERIN; PANTHENOL; POLYETHYLENE GLYCOL 400; PPG-14 PALMETH-60 HEXYL DICARBAMATE; HYALURONATE SODIUM; TROLAMINE; WATER

Dermesse Benzoyl Peroxide 5% Gel

Active Ingredient:

Benzoyl Peroxide 5%

Purpose

Acne Treatment

USES:

For the treatment of acne.

WARNINGS:

For external use only.

Do not use if you:

• Have sensitive skin. • Are sensitive to benzoyl peroxide.

When using the product:

• Skin irritation and dryness is more likely to occur if you use another topical acne medication at the same time. If this occurs only use one topical acne medication at a time • Avoid unnecessary sun exposure and use a sunscreen • Avoid contact with the eyes, lips, and mouth • Avoid contact with hair and dyed fabrics which may be bleached by this product • Skin irritation may occur characterized by redness, burning, itching, peeling, or possibly swelling. Irritation may be reduced by using the product less frequently or in a lower concentration.

Stop use and ask a doctor if:

Irritation become severe.

Keep out of reach of children.

If swallowed get medical help or contact a Poison Control Center right away.

DIRECTIONS:

• Clean the skin thoroughly before applying this product • Cover the entire affected area with a thin layer one to three times daily • Because excessive drying of the skin may occur, start with one application daily, then gradually increase to two to three times daily if needed or as directed by a doctor • If bothersome dryness or peeling occurs, reduce application to once a day or every other day • If going outside, apply sunscreen after using this product. If irritation or sensitivity develops, stop use of both products and ask a doctor.

Inactive Ingredients:

Allantoin, Aloe Barbadensis Leaf Extract, Benzyl Alcohol, Carbomer, Disodium EDTA, Disodium Laureth Sulfosuccinate, Glycerin, Panthenol, PEG-8, PEG-14 Palmeth-60 Hexyl Dicarbamate, Sodium Hyaluronate, Triethanolamine, and Water.

OTHER INFORMATION:

• Store at controlled room temperature 15-30°C (59-86°F)

Questions?:

866-494-4466, Mon-Fri 8:00AM-5:00PM

Dist. By Axia Medical Solutions, 2105 Camino Vida Roble, Carlsbad, Ca. 92011

www.dermesse.com 866-494-4466 office, 760-931-8267 fax